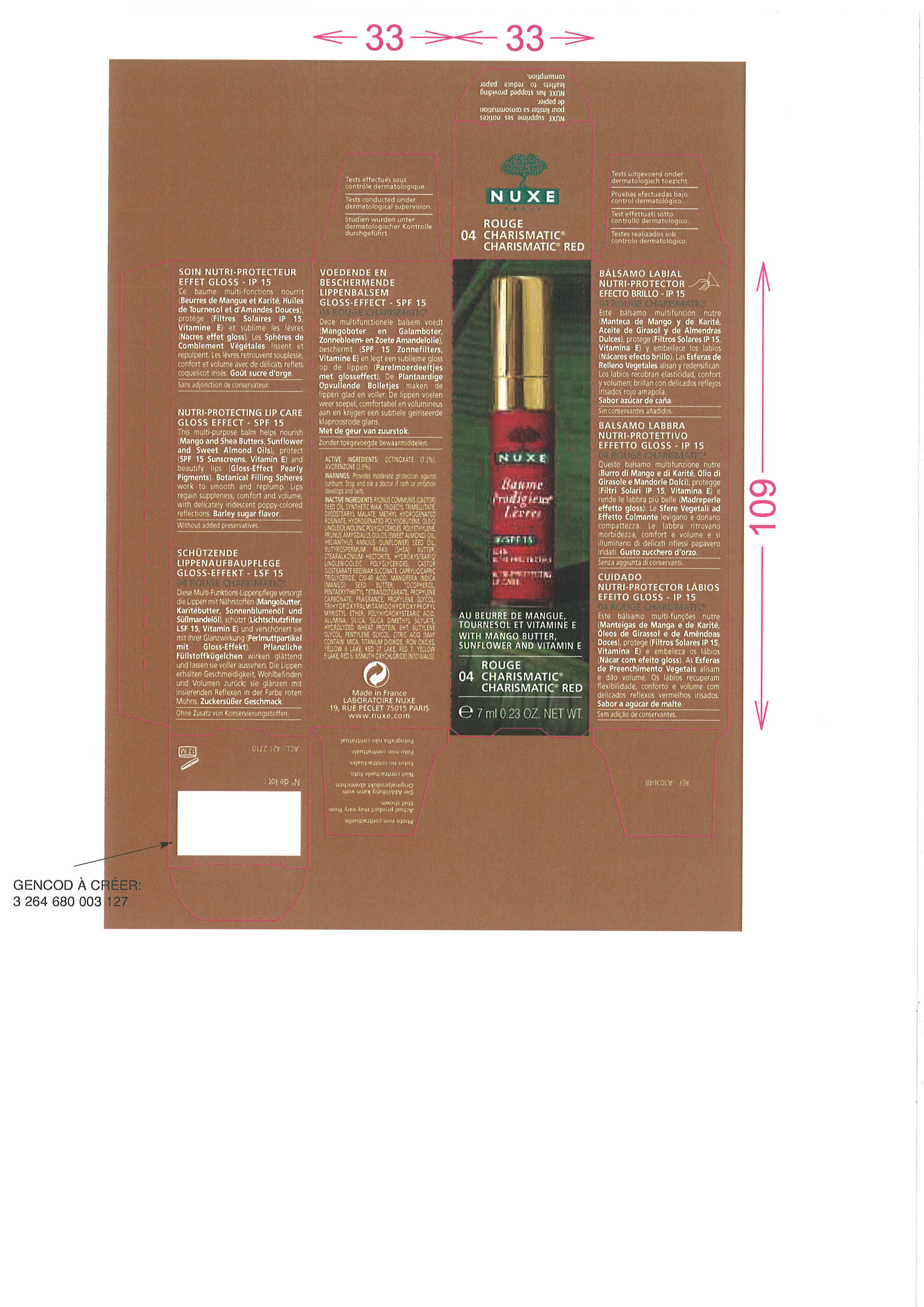 DRUG LABEL: BAUME PRODIGIEUX LEVRES 04 RED CHARISMATIC
NDC: 67542-040 | Form: LIPSTICK
Manufacturer: LABORATOIRE NUXE
Category: otc | Type: HUMAN OTC DRUG LABEL
Date: 20091201

ACTIVE INGREDIENTS: OCTINOXATE 7.3 mL/100 mL; AVOBENZONE 2.9 mL/100 mL
INACTIVE INGREDIENTS: CASTOR OIL; SYNTHETIC WAX (1200 MW); TRIDECYL TRIMELLITATE; HYDROGENATED POLYBUTENE (1300 MW); DIISOSTEARYL MALATE; HIGH DENSITY POLYETHYLENE; ALMOND OIL; SUNFLOWER OIL; SHEA BUTTER; MEDIUM-CHAIN TRIGLYCERIDES; C20-40 ACID; MANGIFERA INDICA SEED BUTTER; TOCOPHEROL; TITANIUM DIOXIDE; PENTAERYTHRITYL TETRAISOSTEARATE; PROPYLENE CARBONATE; MICA; D&C RED NO. 6; D&C RED NO. 7; TRIHYDROXYPALMITAMIDOHYDROXYPROPYL MYRISTYL ETHER; POLYHYDROXYSTEARIC ACID (2300 MW); ALUMINUM OXIDE; SILICON DIOXIDE; FERRIC OXIDE RED; SILICA DIMETHYL SILYLATE; HYDROLYZED WHEAT PROTEIN (ENZYMATIC, 3000 MW); BUTYLATED HYDROXYTOLUENE; BUTYLENE GLYCOL; PENTYLENE GLYCOL; CITRIC ACID MONOHYDRATE

Drug Facts

PACKAGE LABEL

ACTIVE INGREDIENTS : OCTINOXATE (7.3%), AVOBENZONE (2.9%)
WARNINGS : Provides moderate protection against sunburn. Stop and ask a doctor if rash or irritation develops and lasts.